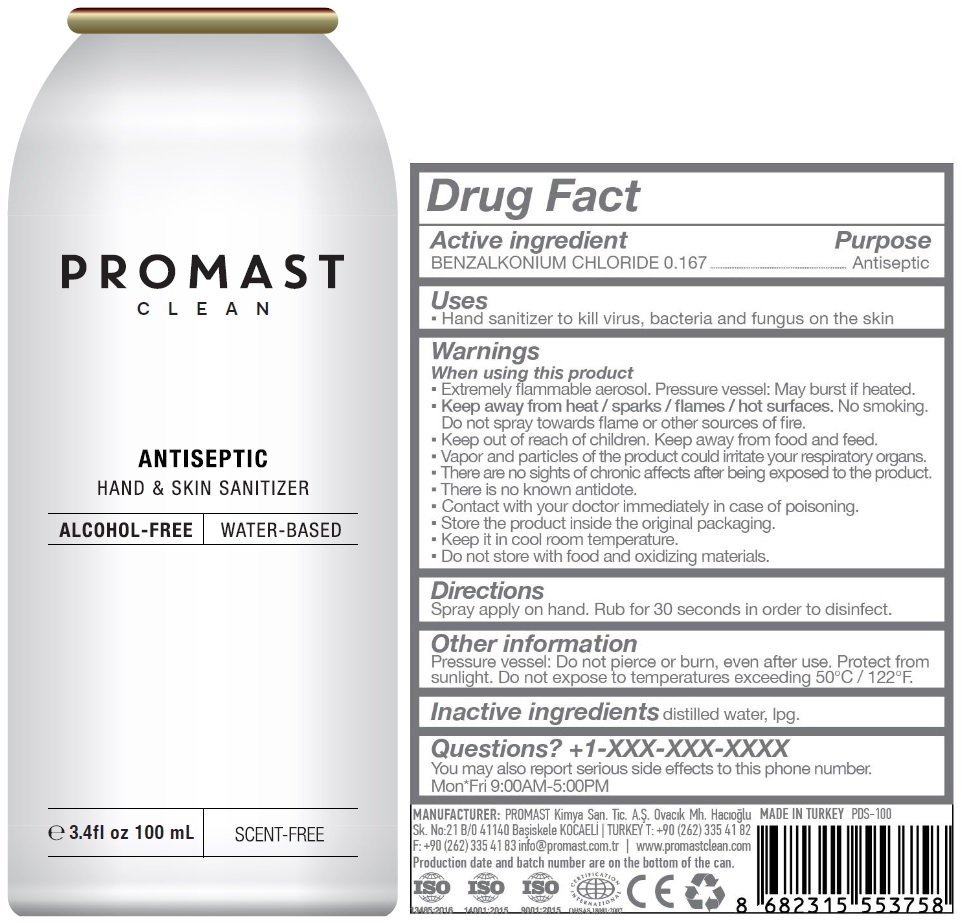 DRUG LABEL: PROMAST CLEAN ANTISEPTIC HAND AND SKIN SANITIZER ALCOHOL-FREE SCENT-FREE
NDC: 81164-103 | Form: AEROSOL, SPRAY
Manufacturer: PROMAST KIMYA SANAYI VE TICARET ANONIM SIRKETI
Category: otc | Type: HUMAN OTC DRUG LABEL
Date: 20201126

ACTIVE INGREDIENTS: BENZALKONIUM CHLORIDE 0.167 g/100 mL
INACTIVE INGREDIENTS: WATER; LIQUEFIED PETROLEUM GAS

PROMAST CLEAN ANTISEPTIC HAND & SKIN SANITIZER

Active ingredient

BENZALKONIUM CHLORIDE 0.167

Purpose

Antiseptic

Uses

• Hand sanitizer to kill virus, bacteria and fungus on the skin

Warnings

When using this product

• Extremely flammable aerosol. Pressure vessel: May burst if heated.

• Keep away from heat / sparks / flames / hot surfaces. No smoking.

Do not spray towards flame or other sources of fire.

• Vapor and particles of the product could irritate your respiratory organs.

• There are no sights of chronic affects after being exposed to the product.

• There is no known antidote.

• Contact with your doctor immediately in case of poisoning.

• Store the product inside the original packaging.

• Keep it in cool room temperature.

• Do not store with food and oxidizing materials.

• Keep out of reach of children. Keep away from food and feed.

Directions

Spray apply on hand. Rub for 30 seconds in order to disinfect.

Other information

Pressure vessel: Do not pierce or burn, even after use. Protect from sunlight. Do not expose to temperatures exceeding 50°C / 122°F.

Inactive ingredients

distilled water, lpg.

Questions? +1-XXX-XXX-XXXX

You may also report serious side effects to this phone number.

Mon*Fri 9:00AM-5:00PM

ALCOHOL-FREE

WATER-BASED

MANUFACTURER: PROMAST Kimya San. Tic. A.Ş Ovacık Mh. Hacıoğlu

Sk. No:21 B/0 41140 Başiskele KOCAELİ | TURKEY T: +90 (262) 335 41 82

F: +90 (262) 335 41 83 info@promast.com.tr | www.promastclean.com

Product date and batch number are on the bottom of the can.

MADE IN TURKEY